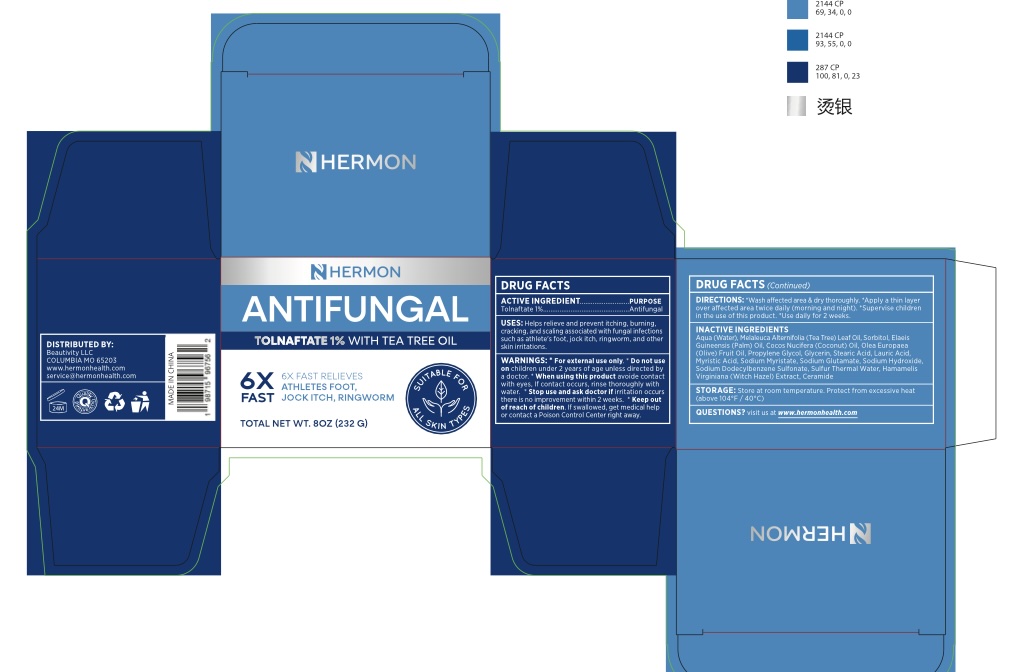 DRUG LABEL: HERMON ANTIFUNGAL BAR
NDC: 85261-601 | Form: SOAP
Manufacturer: Haikou Pucao Trading Co.,Ltd
Category: otc | Type: HUMAN OTC DRUG LABEL
Date: 20260114

ACTIVE INGREDIENTS: TOLNAFTATE 1 g/100 g
INACTIVE INGREDIENTS: MELALEUCA ALTERNIFOLIA (TEA TREE) LEAF OIL; WATER; LAURIC ACID; PROPYLENE GLYCOL STEARATE; BUTYROSPERMUM PARKII (SHEA) BUTTER; SODIUM HYDROXIDE; COCOS NUCIFERA (COCONUT) OIL; STEARIC ACID; SORBITOL; ALOE BARBADENSIS LEAF JUICE; FRAGRANCE LAVENDER ORC1800979; GLYCERIN; SODIUM PALMITATE; SUCROSE

85261-601 - 激活

ACTIVE INGREDIENT

Tolnaftate 1%

PURPOSE

Antifungal

WARNINGS

For External use only.

Do not use on Children under 2 years of age unless directed by a doctor.

When using this product avoid contact with eyes, if contact occurs, rinse thoroughly with water.

Stop use and ask doctor if irritation occurs or there is no improvement within 2 weeks.

keep out of reach of Children. If swallowed, get medical help of contac a Poison Control Center right away.

OTHER SAFETY INFORMATION

Store at room temperature. Protect from excessive heat (above 104°F/ 40°C)

DOSAGE AND ADMINISTRATION

Wash affected area & dry thoroughly. Apply a thin layer over affected area twice daily (morning and night). Supervise children in the use of this product. Use daily for 2 weeks.

INACTIVE INGREDIENT

Stearic Acid, Lauric Acid, Water, Cocos Nucifera (Coconut) Oil, Glycerin, Sorbitol, Sucrose, Aloe Barbadensis Leaf Juice, Sodium Palmitate, Melaleuca Alternifolia (Tea Tree) Leaf Oil, Butyrospermum Parkii (Shea) Butter, Sodium Hydroxide, Propylene Glycol Stearate, Fragrance Lavender

INDICATIONS AND USAGE

Helps relieve and prevent itching, burning, cracking, and scaling associated with fungal infections such as athlete's foot, jock itch, ringworm, and other skin irriations.